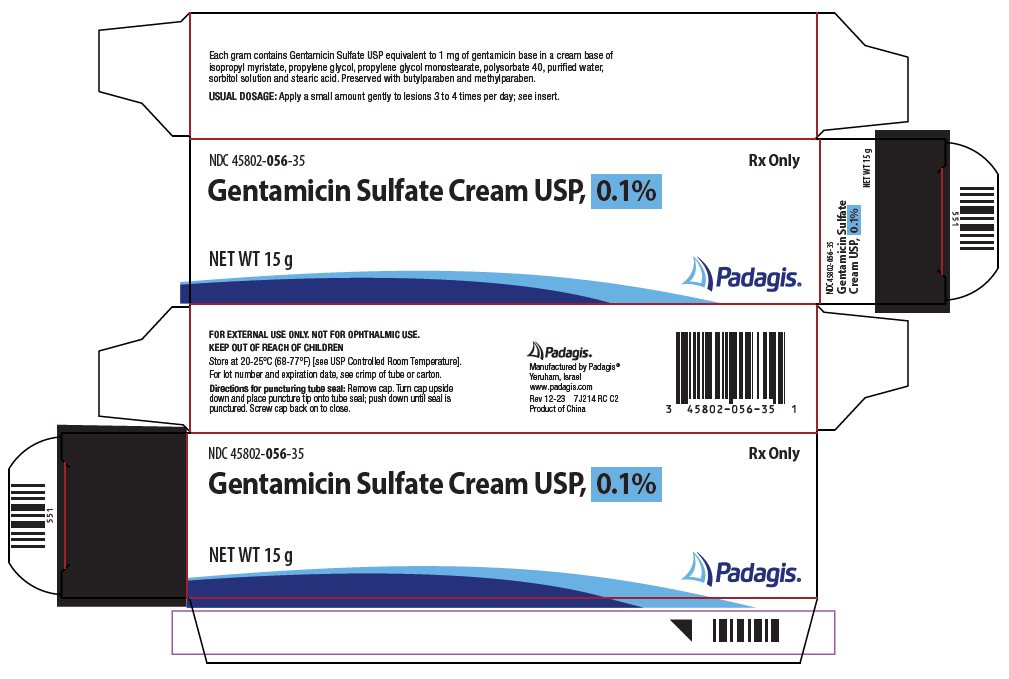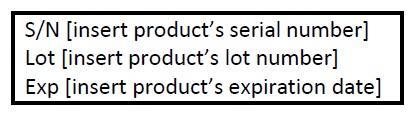 DRUG LABEL: Gentamicin Sulfate
NDC: 45802-056 | Form: CREAM
Manufacturer: Padagis Israel Pharmaceuticals Ltd
Category: prescription | Type: HUMAN PRESCRIPTION DRUG LABEL
Date: 20230131

ACTIVE INGREDIENTS: GENTAMICIN SULFATE 1 mg/1 g
INACTIVE INGREDIENTS: ISOPROPYL MYRISTATE; PROPYLENE GLYCOL; PROPYLENE GLYCOL MONOPALMITOSTEARATE; POLYSORBATE 40; WATER; SORBITOL; STEARIC ACID; METHYLPARABEN; BUTYLPARABEN

Gentamicin Sulfate Cream USP, 0.1%

Rx Only

For Dermatologic Use Only

Not For Ophthalmic Use

DESCRIPTION

Gentamicin Sulfate Cream USP, 0.1% is a wide spectrum antibiotic preparation for topical administration. Each gram of Gentamicin Sulfate Cream USP, 0.1% contains Gentamicin Sulfate USP equivalent to 1 mg of gentamicin base in a cream base of isopropyl myristate, propylene glycol, propylene glycol monostearate, polysorbate 40, purified water, sorbitol solution, and stearic acid, with methylparaben and butylparaben as preservatives.

CLINICAL PHARMACOLOGY

Gentamicin Sulfate is a wide spectrum antibiotic that provides highly effective topical treatment in primary and secondary bacterial infections of the skin. Gentamicin Sulfate Cream USP, 0.1% may clear infections that have not responded to other topical antibiotic agents. In primary skin infections such as impetigo contagiosa, treatment three or four times daily with Gentamicin Sulfate Cream USP, 0.1% usually clears the lesions promptly. In secondary skin infections, Gentamicin Sulfate Cream USP, 0.1% aids in the treatment of the underlying dermatosis by controlling the infection. Bacteria susceptible to the action of gentamicin sulfate include sensitive strains of Streptococci (group A beta-hemolytic, alpha-hemolytic), Staphylococcus aureus (coagulase positive, coagulase negative, and some penicillinase-producing strains), and the gram-negative bacteria, Pseudomonas aeruginosa, Aerobacter aerogenes, Escherichia coli, Proteus vulgaris and Klebsiella pneumoniae.

INDICATIONS AND USAGE

Primary skin infections: Impetigo contagiosa, superficial folliculitis, ecthyma, furunculosis, sycosis barbae, and pyoderma gangrenosum. Secondary skin infections: Infectious eczematoid dermatitis, pustular acne, pustular psoriasis, infected seborrheic dermatitis, infected contact dermatitis (including poison ivy), infected excoriations, and bacterial superinfections of fungal or viral infections. Please Note: Gentamicin Sulfate is a bactericidal agent that is not effective against viruses or fungi in skin infections. It is useful in the treatment of infected skin cysts and certain other skin abscesses when preceded by incision and drainage to permit adequate contact between the antibiotic and the infecting bacteria. Good results have been obtained in the treatment of infected stasis and other skin ulcers, infected superficial burns, paronychia, infected insect bites and stings, infected lacerations and abrasions, and wounds from minor surgery. Patients sensitive to neomycin can be treated with Gentamicin Sulfate, although regular observation of patients sensitive to topical antibiotics is advisable when such patients are treated with any topical antibiotic. Gentamicin Sulfate Cream USP, 0.1% is recommended for wet, oozing primary infections, and greasy, secondary infections, such as pustular acne or infected seborrheic dermatitis. Gentamicin sulfate ointment helps retain moisture and has been useful in infection on dry eczematous or psoriatic skin. If a water-washable preparation is desired, the cream is preferable. Gentamicin Sulfate Cream USP, 0.1% has been used successfully in infants over one year of age, as well as in adults and children.

CONTRAINDICATIONS

This drug product is contraindicated in individuals with a history of sensitivity to any of its components.

PRECAUTIONS

The use of topical antibiotics occasionally allows overgrowth of nonsusceptible organisms, including fungi. If this occurs, or if irritation, sensitization, or superinfection develops, treatment with Gentamicin Sulfate should be discontinued and appropriate therapy instituted.

ADVERSE REACTIONS

In patients with dermatoses treated with Gentamicin Sulfate, irritation (erythema and pruritus) that did not usually require discontinuance of treatment has been reported in a small percentage of cases. There was no evidence of irritation or sensitization, however, in any of these patients patch-tested subsequently with Gentamicin Sulfate on normal skin. Possible photosensitization has been reported in several patients but could not be elicited in these patients by reapplication of Gentamicin Sulfate followed by exposure to ultraviolet radiation.

DOSAGE AND ADMINISTRATION

A small amount of Gentamicin Sulfate Cream USP, 0.1% should be applied gently to lesions three or four times a day. The area treated may be covered with a gauze dressing if desired. In impetigo contagiosa, the crusts should be removed before application of Gentamicin Sulfate Cream USP, 0.1% to permit maximum contact between the antibiotic and the infection. Care should be exercised to avoid further contamination of the infected skin. Infected stasis ulcers have responded well to Gentamicin Sulfate under gelatin packing.

HOW SUPPLIED

Gentamicin Sulfate Cream USP, 0.1% is available as follows:

15 g tube (NDC 45802-056-35)

30 g tube (NDC 45802-056-11)

STORAGE

Store at 20-25°C (68-77°F) [see USP Controlled Room Temperature].

Manufactured by Padagis®

Yeruham, Israel

www.padagis.com

Rev 01-23

7J200 RC PH1

Principal Display Panel - 15 g Cream Carton

NDC 45802-056-35

Rx Only

Gentamicin Sulfate Cream USP, 0.1%

NET WT 15 g

The following image is a placeholder representing the product identifier that is either affixed or imprinted on the drug package label during the packaging operation.